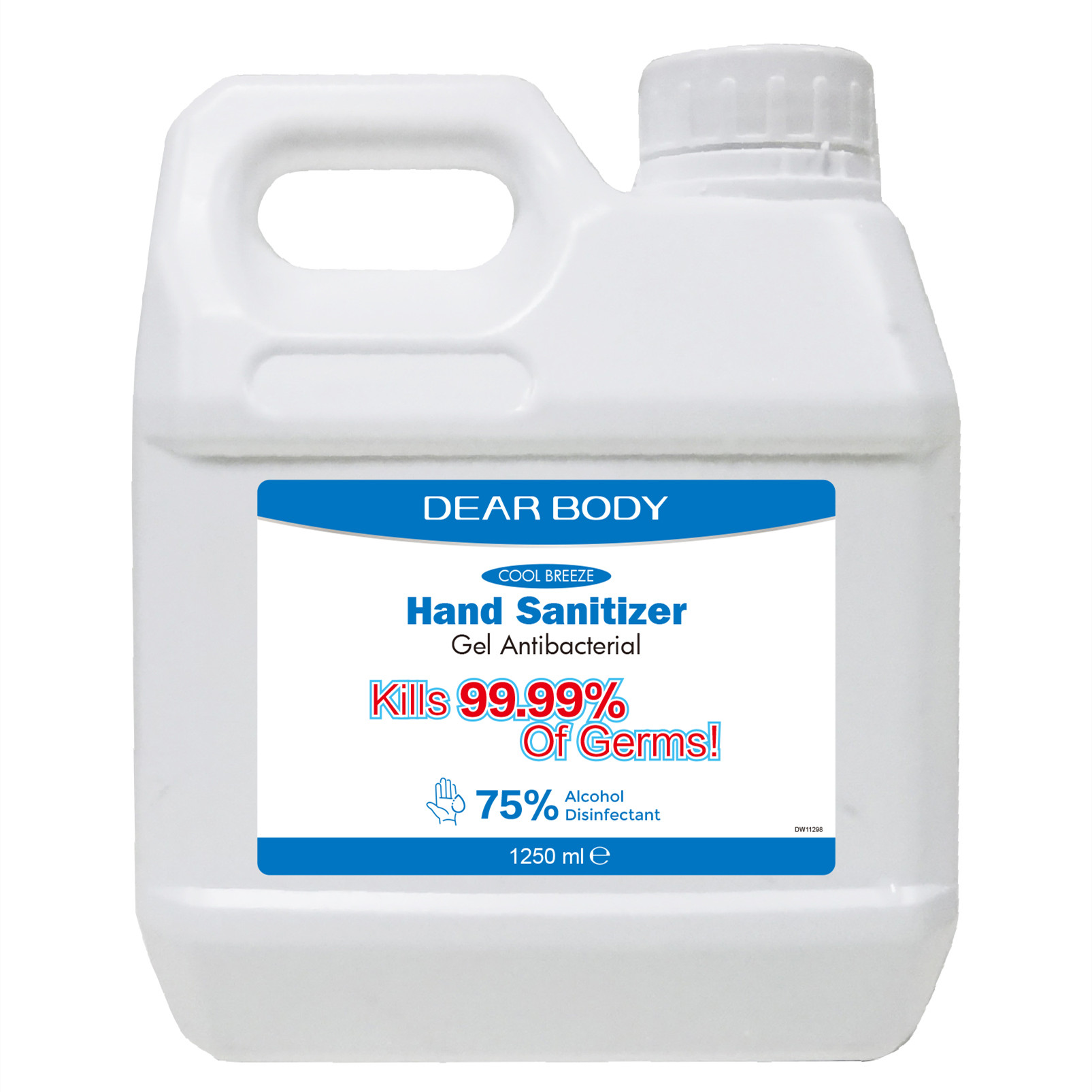 DRUG LABEL: Hand Sanitizer
NDC: 41366-009 | Form: GEL
Manufacturer: Zhejiang Meimi Technology Co., Ltd.
Category: otc | Type: HUMAN OTC DRUG LABEL
Date: 20200422

ACTIVE INGREDIENTS: ALCOHOL 937.5 mL/1250 mL
INACTIVE INGREDIENTS: FRAGRANCE LAVENDER & CHIA F-153480; 2-(2-(2-HYDROXYPROPOXY)PROPOXY)-1-PROPANOL; .ALPHA.-TOCOPHEROL ACETATE; EDETATE DISODIUM ANHYDROUS; LINALOOL, (+)-; CARBOMER HOMOPOLYMER TYPE B (ALLYL SUCROSE CROSSLINKED); WATER

DOSAGE AND ADMINISTRATION

Keep away from flame or high heat.

INACTIVE INGREDIENT

Water(Aqua, Eau.)

Propylene Glycol

Carbomer

Fragrance (Parfum)

Tocopheryl Acetate

DISODIUM EDTA

Linalool

INDICATIONS AND USAGE

Put enough product in your palm to cover hands and rub hands together briskly until dry Children should be supervised when using Hand Sanitizer.

ACTIVE INGREDIENT

alcohol

keep out of children

PURPOSE

Disinfection
Sterilization

WARNINGS

Keep away from flame or high heat.